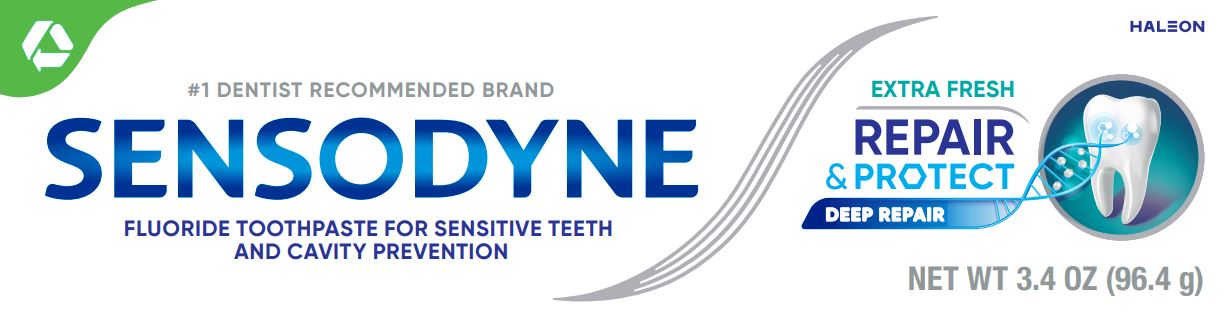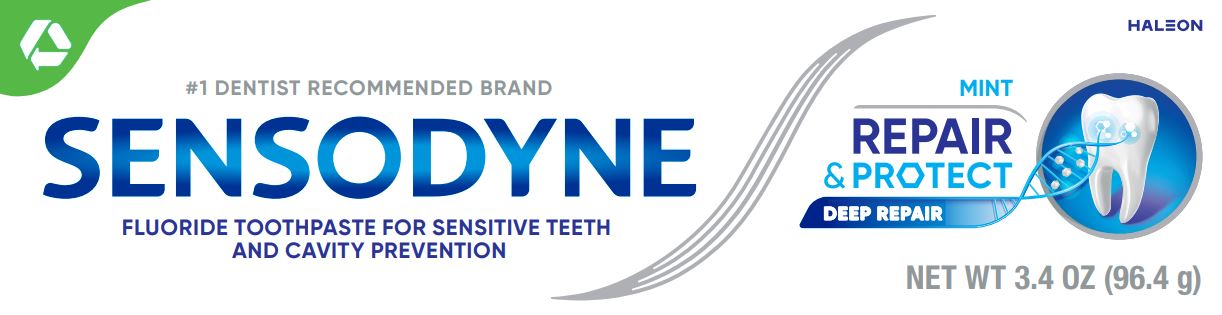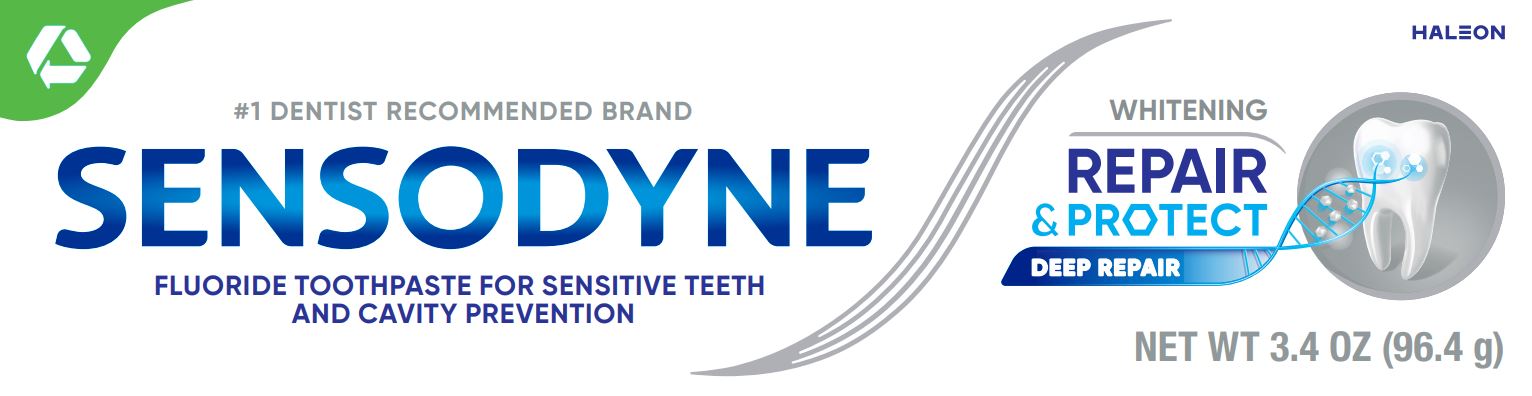 DRUG LABEL: SENSODYNE

NDC: 0135-0548 | Form: PASTE
Manufacturer: Haleon US Holdings LLC
Category: otc | Type: HUMAN OTC DRUG LABEL
Date: 20240306

ACTIVE INGREDIENTS: STANNOUS FLUORIDE 1.1 mg/1 g
INACTIVE INGREDIENTS: GLYCERIN; POLYETHYLENE GLYCOL 400; HYDRATED SILICA; SODIUM TRIPOLYPHOSPHATE, UNSPECIFIED FORM; SODIUM LAURYL SULFATE; TITANIUM DIOXIDE; SILICON DIOXIDE; COCAMIDOPROPYL BETAINE; SACCHARIN SODIUM

Drug Facts

Active ingredient

Stannous fluoride 0.454% (0.15% w/v fluoride ion)

Purposes

Anticavity, Antihypersensitivity

Uses

- aids in the prevention of dental cavities.
- builds increasing protection against painful sensitivity of the teeth to cold, heat, acids, sweets or contact.

Warnings

Stop use and ask a dentist if

- the problem persists or worsens. Sensitive teeth may indicate a serious problem that may need prompt care by a dentist.
- pain/sensitivity still persists after 4 weeks of use.

Keep out of reach of children.

If more than used for brushing is accidentally swallowed, get medical help or contact a Poison Control Center right away.

Directions

- adults and children 12 years of age and older:
  - apply at least a 1-inch strip of the product onto a soft bristle toothbrush.
  - brush teeth thoroughly for at least 1 minute twice a day (morning and evening), and not more than 3 times a day, or as recommended by a dentist or doctor. Make sure to brush all sensitive areas of the teeth. Minimize swallowing. Spit out after brushing.
- children under 12 years of age:Consult a dentist or doctor.

Other information

- products containing stannous fluoride may product surface staining of the teeth. Adequate toothbrushing may prevent these stains which are not harmful or permanent and may be removed by your dentist.
- this product is specifically formulated to help prevent staining.
- store above 30°C (86°F)

Inactive ingredients (Mint)

glycerin, PEG-8, hydrated silica, pentasodium triphosphate, flavor, sodium lauryl sulfate, titanium dioxide, polyacrylic acid, silica, cocamidopropyl betaine, sodium saccharin

Inactive ingredients (Extra Fresh)

glycerin, PEG-8, hydrated silica, pentasodium triphosphate, flavor, sodium lauryl sulfate, titanium dioxide, polyacrylic acid, silica, sodium saccharin, cocamidopropyl betaine

Inactive ingredients (Whitening)

glycerin, PEG-8, hydrated silica, pentasodium triphosphate, flavor, sodium lauryl sulfate, titanium dioxide, polyacrylic acid, silica, cocamidopropyl betaine, sodium saccharin

Questions or comments?

1-866-844-2797

Other Information

SENSODYNE REPAIR & PROTECT DEEP REPAIR

Sensodyne Repair & Protecthas a clinically proven ingredient. With twice daily brushing it helps to repair deep inside the tubules and relieves sensitivity to help you enjoy life without worrying about the pain of sensitive teeth.

EXPOSED DENTIN; CAUSE OF SENSITIVE TEETH

TINY HOLES

GETS DEEP INSIDE THESE HOLES

TO HELP REPAIR THESE HOLES

WHICH HELPS PROTECT FROM PAIN*

Daily use fluoride toothpaste to provide long lasting sensitivity relief, whilst also keeping your teeth and gums healthy. *

*with twice daily brushing

Trademarks are owned by or licensed to the Haleon group of companies.

©2023 Haleon group of companies or its licensor.

Distributed by: Haleon, Warren, NJ 07059

Pat. Info www.productpats.com

†Recycling facilities for this product may not exist in your area

CARTONRECYCLE

TUBERECYCLE

CAPCHECK LOCALLY†

Principal Display Panel (Mint)

#1 DENTIST RECOMMENDED BRAND

SENSODYNE

FLUORIDE TOOTHPASTE FOR SENSITIVE TEETH AND CAVITY PREVENTION

MINT

REPAIR & PROTECT

DEEP REPAIR

NET WT 3.4 OZ (96.4 g)

62000000207021

Principal Display Panel (Extra Fresh)

#1 DENTIST RECOMMENDED BRAND

SENSODYNE

FLUORIDE TOOTHPASTE FOR SENSITIVE TEETH AND CAVITY PREVENTION

EXTRA FRESH

REPAIR & PROTECT

DEEP REPAIR

NET WT 3.4 OZ (96.4 g)

62000000207114

Principal Display Panel (Whitening)

#1 DENTIST RECOMMENDED BRAND

SENSODYNE

FLUORIDE TOOTHPASTE FOR SENSITIVE TEETH AND CAVITY PREVENTION

WHITENING

REPAIR & PROTECTED

DEEP REPAIR

NET WT 3.4 OZ (96.4 g)

62000000207026